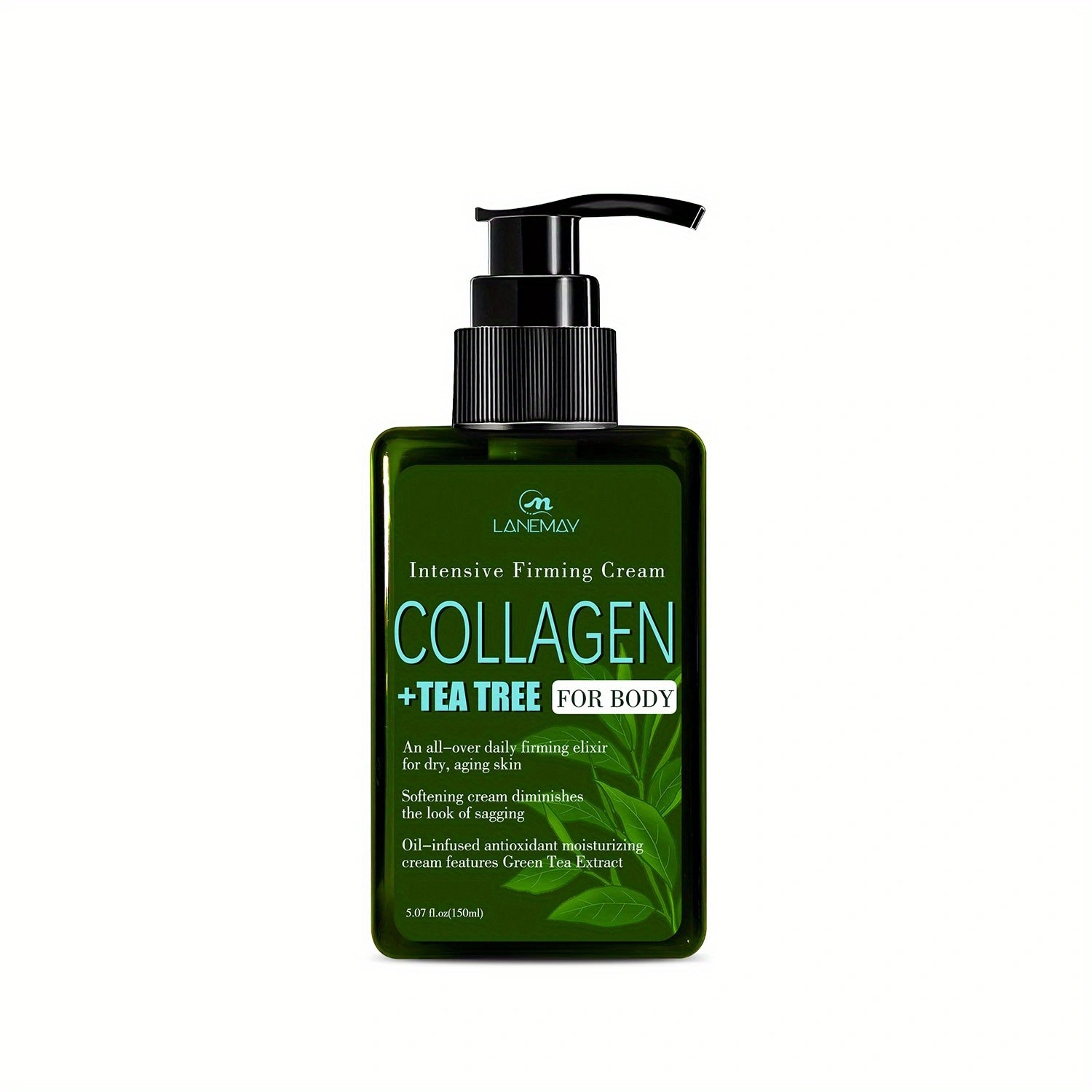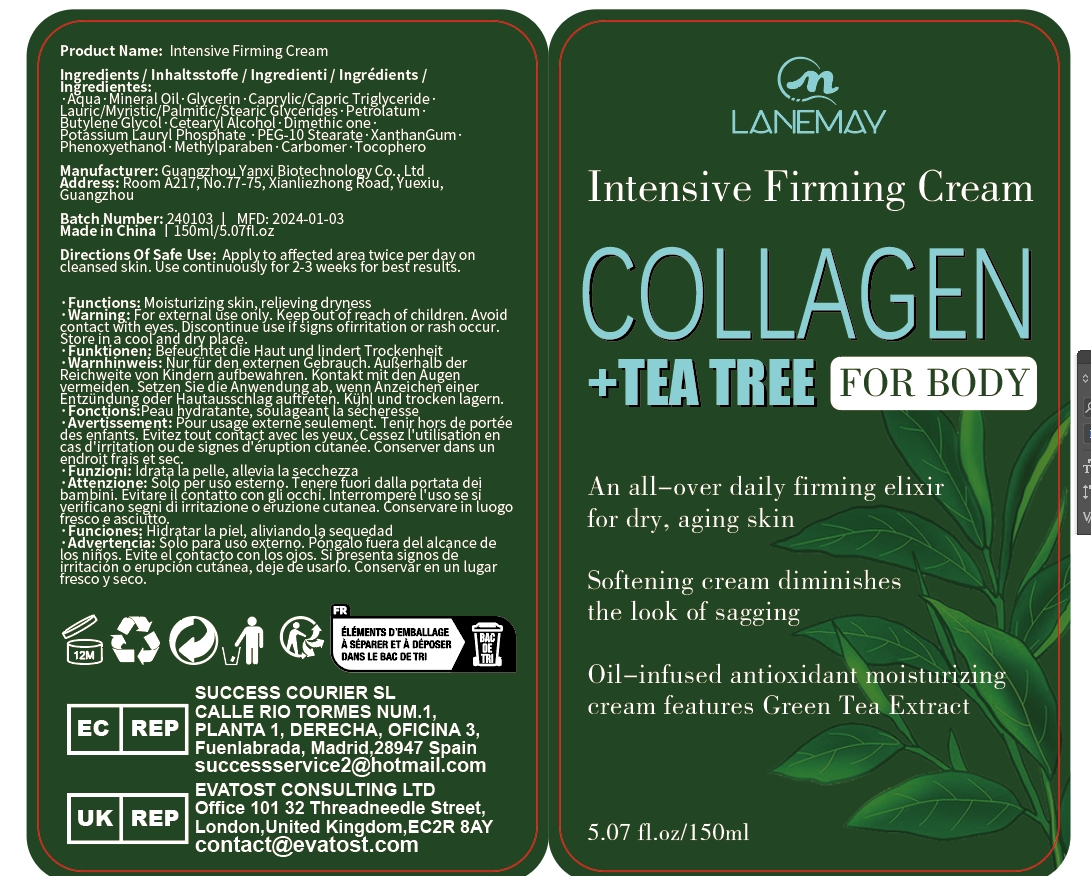 DRUG LABEL: Intensive Firming Cream
NDC: 84025-037 | Form: CREAM
Manufacturer: Guangzhou Yanxi Biotechnology Co., Ltd
Category: otc | Type: HUMAN OTC DRUG LABEL
Date: 20240511

ACTIVE INGREDIENTS: GLYCERIN 3 mg/100 mL; MINERAL OIL 5 mg/100 mL
INACTIVE INGREDIENTS: WATER

DOSAGE AND ADMINISTRATION

Apply to affected area twice per day on cleansed skin. Use continuously for 2-3 weeks for best results.

WARNINGS

For external use only.

INACTIVE INGREDIENT

Aqua

INDICATIONS AND USAGE

Apply to affected area twice per day on cleansed skin.

Keep out of reach of children.

PURPOSE

Moisturizing skin, relieving dryness.